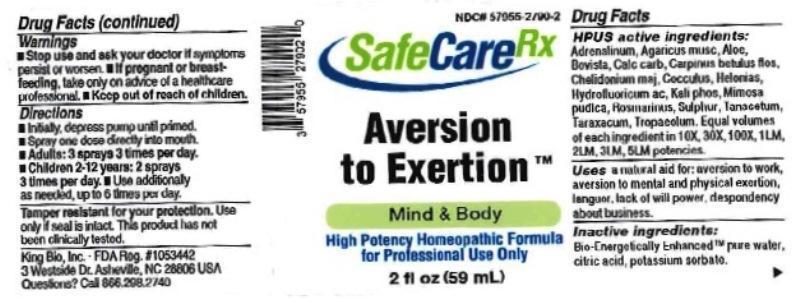 DRUG LABEL: Aversion to Exertion
NDC: 57955-2790 | Form: LIQUID
Manufacturer: King Bio Inc.
Category: homeopathic | Type: HUMAN OTC DRUG LABEL
Date: 20170214

ACTIVE INGREDIENTS: EPINEPHRINE 10 [hp_X]/59 mL; AMANITA MUSCARIA FRUITING BODY 10 [hp_X]/59 mL; ALOE 10 [hp_X]/59 mL; LYCOPERDON UTRIFORME FRUITING BODY 10 [hp_X]/59 mL; OYSTER SHELL CALCIUM CARBONATE, CRUDE 10 [hp_X]/59 mL; CARPINUS BETULUS FLOWERING TOP 10 [hp_X]/59 mL; CHELIDONIUM MAJUS 10 [hp_X]/59 mL; ANAMIRTA COCCULUS SEED 10 [hp_X]/59 mL; CHAMAELIRIUM LUTEUM ROOT 10 [hp_X]/59 mL; HYDROFLUORIC ACID 10 [hp_X]/59 mL; POTASSIUM PHOSPHATE, DIBASIC 10 [hp_X]/59 mL; MIMOSA PUDICA LEAF 10 [hp_X]/59 mL; ROSMARINUS OFFICINALIS FLOWERING TOP 10 [hp_X]/59 mL; SULFUR 10 [hp_X]/59 mL; TANACETUM VULGARE TOP 10 [hp_X]/59 mL; TARAXACUM OFFICINALE 10 [hp_X]/59 mL; TROPAEOLUM MAJUS 10 [hp_X]/59 mL
INACTIVE INGREDIENTS: WATER; ANHYDROUS CITRIC ACID; POTASSIUM SORBATE

Aversion to Exertion

Drug Facts

___________________________________________________________________________________________________________________

HPUS active ingredients: Adrenalinum, Agaricus muscarius, Aloe socotrina, Bovista, Calcarea carbonica, Carpinus betulus, flos, Chelidonium majus, Cocculus indicus, Helonias dioica, Hydrofluoricum acidum, Kali phosphoricum, Mimosa pudica, Rosmarinus officinalis, Sulphur, Tanacetum vulgare, Taraxacum officinale, Tropaeolum majus. Equal volumes of each ingredient in 10X, 30X, 100X, 1LM, 2LM, 3LM, 5LM potencies.

INDICATIONS AND USAGE

Uses a natural aid for: aversion to work, aversion to mental and/or physical exertion, languor, lack of will power, despondency about business.

INACTIVE INGREDIENT

Inactive ingredients: Bio-Energetically Enhanced™ pure water, citric acid, potassium sorbate.

Warnings

- Stop use and ask your doctor if symptoms persist or worsen.
- If pregnant or breast-feeding, take only on advice of a healthcare professional.

- Keep out of reach of children.

Directions

- Initially, depress pump until primed.
- Spray one dose directly into mouth.
- Adults: 3 sprays 3 times per day.
- Children 2-12 years: 2 sprays 3 times per day.
- Use additionally as needed, up to 6 times per day.

OTHER SAFETY INFORMATION

Tamper resistant for your protection. Use only if safety seal is intact. This product has not been clinically tested.

PURPOSE

Use a natural aid for:

- aversion to work
- aversion to mental and/or physical exertion
- languor
- lack of will power
- despondency about business